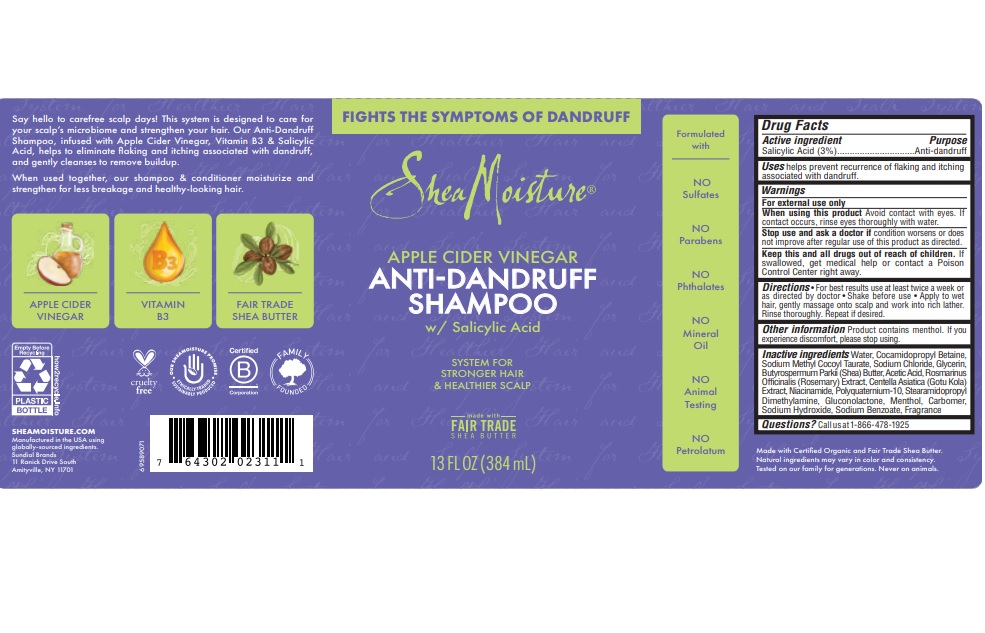 DRUG LABEL: Shea Moisture
NDC: 64942-2082 | Form: LIQUID
Manufacturer: Conopco, Inc. d/b/a/ Unilever
Category: otc | Type: HUMAN OTC DRUG LABEL
Date: 20241107

ACTIVE INGREDIENTS: SALICYLIC ACID 3 g/100 mL
INACTIVE INGREDIENTS: SODIUM BENZOATE; SODIUM HYDROXIDE; WATER; COCAMIDOPROPYL BETAINE; SODIUM CHLORIDE; SODIUM METHYL COCOYL TAURATE; GLYCERIN; SHEA BUTTER; GLUCONOLACTONE; ROSEMARY; ACETIC ACID; NIACINAMIDE; STEARAMIDOPROPYL DIMETHYLAMINE; MENTHOL; CARBOMER HOMOPOLYMER, UNSPECIFIED TYPE

Shea Moisture Apple Cider Vinegar Anti-dandruff Shampoo

Drug Facts

Active ingredient

Salicylic Acid (3%)

Purpose

Anti-dandruff

Uses

helps prevent recurrence of itching and flaking associated with dandruff.

Warnings

For external use only
When using this product avoid contact with eyes. If contact occurs, rinse eyes thoroughtly with water.
Stop use and ask a doctor if condition worsens or does not improve after regular use of this product as directed.

KEEP OUT OF REACH OF CHILDREN

Keep this and all drugs out of reach of children.
If swallowed, get medical help or contact a Poison Control Center right away.

Directions

For best results use at least twice a week or as directed by doctor. Shake well before use. Apply to wet hair, gently massage onto scalp and work into rich lather. Rinse thoroughly. Repeat if desired.

Other information

Product contains menthol. If you experience discomfort, please stop using.

Inactive Ingredients

Water, Cocamidopropyl Betaine, Sodium Methyl Cocoyl Taurate, Sodium Chloride, Glycerin, Butyrospermum Parkii (Shea) Butter, Acetic Acid, Rosmarinus Officinalis (Rosemary) Extract, Centella Asiatica (Gotu Kola) Extract, Niacinamide, Polyquaternium-10, Stearamidopropyl Dimethylamine, Gluconolactone, Menthol, Carbomer, Sodium Hydroxide, Sodium Benzoate, Fragrance

Questions?

Call us at 1-866-478-1925